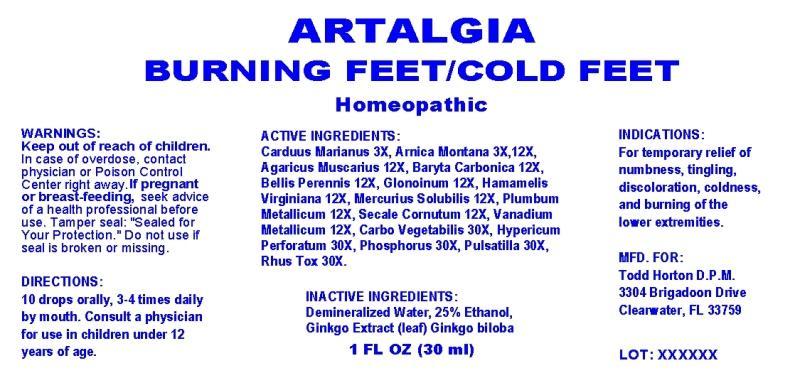 DRUG LABEL: Artalgia
NDC: 45341-0001 | Form: LIQUID
Manufacturer: Todd Horton DPM
Category: homeopathic | Type: HUMAN OTC DRUG LABEL
Date: 20260112

ACTIVE INGREDIENTS: SILYBUM MARIANUM SEED OIL 3 [hp_X]/1 mL; ARNICA MONTANA 3 [hp_X]/1 mL; AMANITA MUSCARIA FRUITING BODY 12 [hp_X]/1 mL; BARIUM CARBONATE 12 [hp_X]/1 mL; BELLIS PERENNIS 12 [hp_X]/1 mL; NITROGLYCERIN 12 [hp_X]/1 mL; HAMAMELIS VIRGINIANA ROOT BARK/STEM BARK 12 [hp_X]/1 mL; MERCURIUS SOLUBILIS 12 [hp_X]/1 mL; LEAD 12 [hp_X]/1 mL; CLAVICEPS PURPUREA SCLEROTIUM 12 [hp_X]/1 mL; VANADIUM 12 [hp_X]/1 mL; ACTIVATED CHARCOAL 30 [hp_X]/1 mL; HYPERICUM PERFORATUM 30 [hp_X]/1 mL; PHOSPHORUS 30 [hp_X]/1 mL; PULSATILLA VULGARIS 30 [hp_X]/1 mL; TOXICODENDRON PUBESCENS LEAF 30 [hp_X]/1 mL
INACTIVE INGREDIENTS: GINKGO; WATER; ALCOHOL

Drug Facts

ACTIVE INGREDIENTS

Carduus Marianus 3X, Arnica Montana 3X, 12X, Agaricus Muscarius 12X, Baryta Carbonica 12X, Bellis Perennis 12X, Glonoinum 12X, Hamamelis Virginiana 12X, Mercurius Solubilis 12X, Plumbum Metallicum 12X, Secale Cornutum 12X, Vanadium Metallicum 12X, Carbo Vegetabilis 30X, Hypericum Perforatum 30X, Phosphorus 30X, Pulsatilla 30X, Rhus Toxicodendron 30X.

INDICATIONS

For temporary relief of numbness, tingling, discoloration, coldness, and burning of the lower extremities.

WARNINGS

Keep out of reach of children. In case of overdose, contact physician or Poison Control Center right away. If pregnant or breast-feeding, seek advice of a health professional before use. Tamper seal: "Sealed for Your Protection." Do not use if seal is broken or missing.

DIRECTIONS

10 drops orally, 3-4 times daily by mouth. Consult a physician for use in children under 12 years of age.

INACTIVE INGREDIENTS

Demineralized Water, 25% Ethanol, Ginkgo Extract (leaf) Ginkgo biloba.

KEEP OUT OF REACH OF CHILDREN

In case of overdose, contact physician or Poison Control Center right away.

INDICATIONS AND USAGE

For temporary relief of numbness, tingling, discoloration, coldness, and burning of the lower extremities.

QUESTIONS

MFD. FOR:

Todd Horton D.P.M.

3304 Brigadoon Drive

Clearwater, FL 33759

PACKAGE LABEL

ARTALGIA

BURNING FEET/COLD FEET

Homeopathic

1 FL OZ (30 ml)